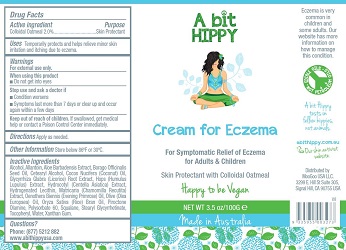 DRUG LABEL: A Bit Hippy
NDC: 70315-001 | Form: CREAM
Manufacturer: A Bit Hippy
Category: homeopathic | Type: HUMAN OTC DRUG LABEL
Date: 20151215

ACTIVE INGREDIENTS: OATMEAL 0.2 g/1 1
INACTIVE INGREDIENTS: RICE BRAN; GREEN OLIVE; ALLANTOIN; CENTELLA ASIATICA; WHEAT BRAN; ALOE VERA FLOWER; BORAGE; AESCULUS HIPPOCASTANUM SEED OIL; CETOSTEARYL ALCOHOL; EUPHORBIA PEKINENSIS ROOT; HOPS; OENOTHERA BIENNIS; ALPHA-TOCOPHERYLQUINONE; COCONUT OIL; GLYCYRRHIZA GLABRA LEAF; HYDROGENATED SOYBEAN LECITHIN; MATRICARIA CHAMOMILLA FLOWERING TOP OIL; ALCOHOL; COCONUT ALCOHOL; PIROCTONE OLAMINE; POLYSORBATE 60; SQUALANE; STEARYL GLYCYRRHETINATE; WATER; DEHYDROXANTHAN GUM

ACTIVE INGREDIENT

Colloidal Oatmeal 2.0%

PURPOSE

Skin protectant

USES Temporarily protects and helps relieve minor skin irritation and itching due to eczema. For Symptomatic relief of Eczema for adult and children.

WARNINGS
For external use only. When using this product do not get into eyes.

Stop use and ask a doctor if condition worsens, symptoms last more than 7 days or clear up and occur again within a few days.

KEEP OUT OF REACH OF CHILDREN
If swallowed, get medical help or contact a Poison Control Center immediately

DOSAGE AND ADMINISTRATION

Apply as needed

OTHER INFORMATION
Store below 86°F or 30°C.

INACTIVE INGREDIENTS
Alcohol, Allantoin, Aloe Barbadensis Extract, Borago Officinalis, Seed Oil, Cetearyl Alcohol, Cocos Nucifera, Coconut Oil,
Glycyrrhiza Glabra (Licorice), Root Extract, Hops Extract (Humulus Lupulus), Hydrocotyl Extract (Centella Asiatica), Hydrogenated Lecithin,
Matricaria (Chamomilla Recutita) Extract, Oenothera Biennis (Evening Primrose)Oil, Olive (Olea Europaea) Oil, Oryza Sativa (Rice) Bran Oil,
Piroctone Olamine, Polysorbate 60, Squalane, Stearyl Glycyrrhetinate, Tocopheryl, Water, Xanthan Gum.

QUESTIONS
Phone (877) 521-2882
www.abithippyusa.com

INDICATIONS AND USAGE

Temporarily protects and helps relieve minor skin irritation and itching due to eczema.

For Symptomatic relief of Eczema for adult and children